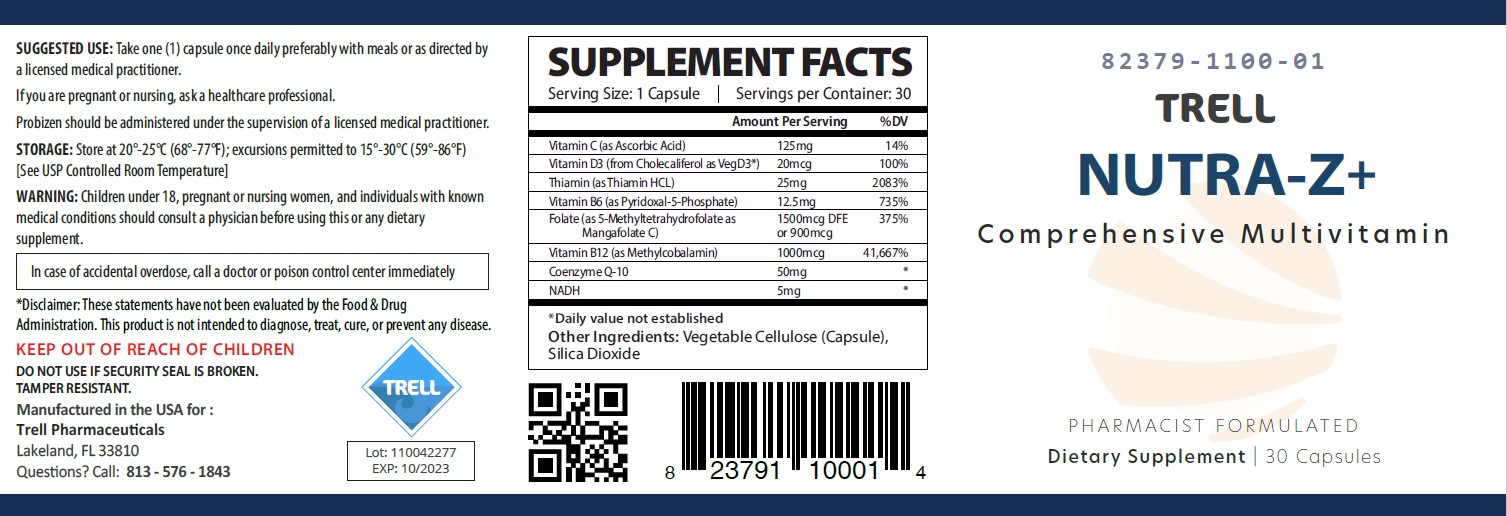 DRUG LABEL: Nutra-Z
NDC: 82379-1100 | Form: CAPSULE
Manufacturer: Trell Pharma
Category: other | Type: DIETARY SUPPLEMENT
Date: 20221023

ACTIVE INGREDIENTS: ASCORBIC ACID 125 mg/1 1; CHOLECALCIFEROL 0.02 mg/1 1; THIAMINE HYDROCHLORIDE 25 mg/1 1; PYRIDOXAL PHOSPHATE ANHYDROUS 12.5 mg/1 1; FOLATE SODIUM 0.9 mg/1 1; METHYLCOBALAMIN 1 mg/1 1; NADH 5 mg/1 1; COENZYME Q10, (2Z)- 50 mg/1 1
INACTIVE INGREDIENTS: SILICON DIOXIDE

Nutra-Z+ Capsules

HEALTH CLAIM:

Nutra-Z+ Dietary Supplement Capsules

Dispensed by Prescription†

Supplement Facts
Serving Size: 1 Tablet
Servings per Bottle: 30
Amount Per Serving: | % Daily Value
Vitamin C (as ascorbic acid) | 125 mg | 208%
Vitamin D3 (as cholecalciferol from Veg D3) | 20 mcg | 100%
Vitamin B1 (as Thiamin HCL) | 25 mg | 2,083%
Vitamin B6 (as Pyridoxal-5-Phosphate) | 12.5 mg | 735%
Folate (as 5-Methyltetrahydrofolate as Magnafolate C) | 900 mcg | 375%
Vitamin B12 (as methylcobalamin) | 1 mg | 41,667%
NADH (reduced nicotinamide-adenine dinucleotide) | 5 mg | *
CoEnzyme Q-10 | 50 mg | *
*Daily Values (DV) not established.

OTHER INGREDIENTS: Vegetable Cellulose (Capsule), Silica Dioxide

WARNING AND PRECAUTIONS

This product is contraindicated in patients with a known hypersensitivity to any of the ingredients.

Nutra-Z+ should only be used under the direction and supervision of a licensed medical practitioner.

WARNING: Children under 18, pregnant or nursing women, and individuals with known medical conditions should consult a physician before using this or any dietary supplement.

In case of accidental overdoes, call a doctor or poison control center immediately.

KEEP OUT OF REACH OF CHILDREN

DOSAGE & ADMINISTRATION

Take one (1) capsule once daily preferably with meals or as directed by medical practitioner.

If you are pregnant or nursing, ask a healthcare professional.

Nutra-Z+ should be administered under the supervision of a licensed medical practitioner.

HOW SUPPLIED HEALTH CLAIM:

Nutra-Z+

Dietary Supplement

NHRIC: 82379-1100-01 *

Bottles contain 30 Capsules

Distributed in the USA by:
Trell Pharma, LLC

*Does not represent these product codes to be National Drug Codes (NDC). Product codes are formatted according to standard industry practice, to meet the formatting requirement by pedigree reporting and supply-chain control including pharmacies.

† The most appropriate way to ensure pedigree reporting consistent with these regulatory guidelines and safety monitoring is to dispense this product by prescription. This is not an Orange Book product. This product may be administered only under a physician’s supervision and all prescriptions using this product shall be pursuant to state statutes as applicable. The ingredients, indication or claims of this product are not to be construed to be drug claims.

*Trell Pharma does not represent these product codes to be National Drug Codes (NDC). Product codes are formatted according to standard industry practice, to meet the formatting requirement by pedigree reporting and supply-chain control including pharmacies.

†† This product is a prescription-folate with or without other dietary ingredients that – due to increased folate levels increased risk associated with masking of B12 deficiency (pernicious anemia) requires administration under the care of a licensed medical practitioner (61 FR 8760).1-3 The most appropriate way to ensure pedigree reporting consistent with these regulatory guidelines and safety monitoring is to dispense this product only by prescription. This is not an Orange Book product. This product may be administered only under a physician’s supervision and all prescriptions using this product shall be pursuant to state statutes as applicable. The ingredients, indication or claims of this product are not to be construed to be drug claims.

1. Federal Register Notice of August 2, 1973 (38 FR 20750)
2. Federal Register Notice of October 17, 1980 (45 FR 69043, 69044)
3. Federal Register Notice of March 5, 1996 (61 FR 8760)

STORAGE AND HANDLING:

Store at 20°-25°C (68°-77°F); excursions permitted to 15°-30°C (59°-86°F).